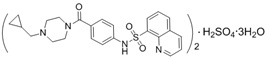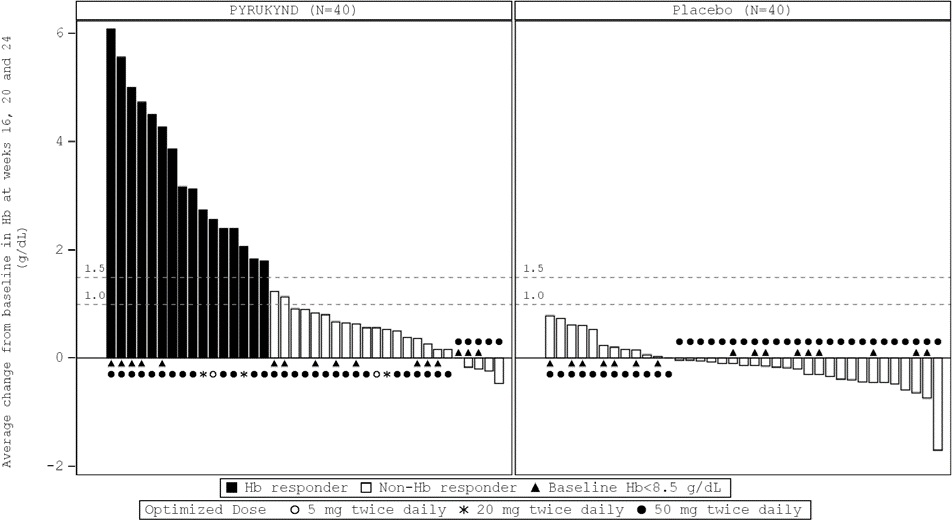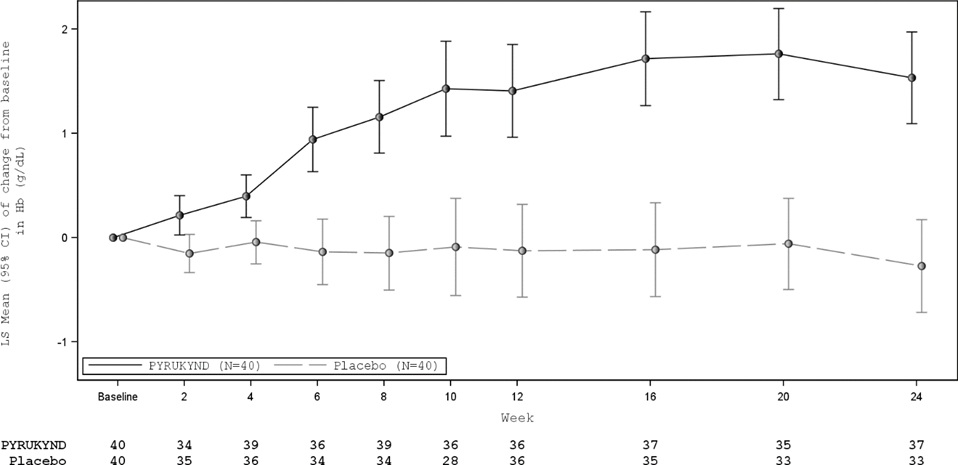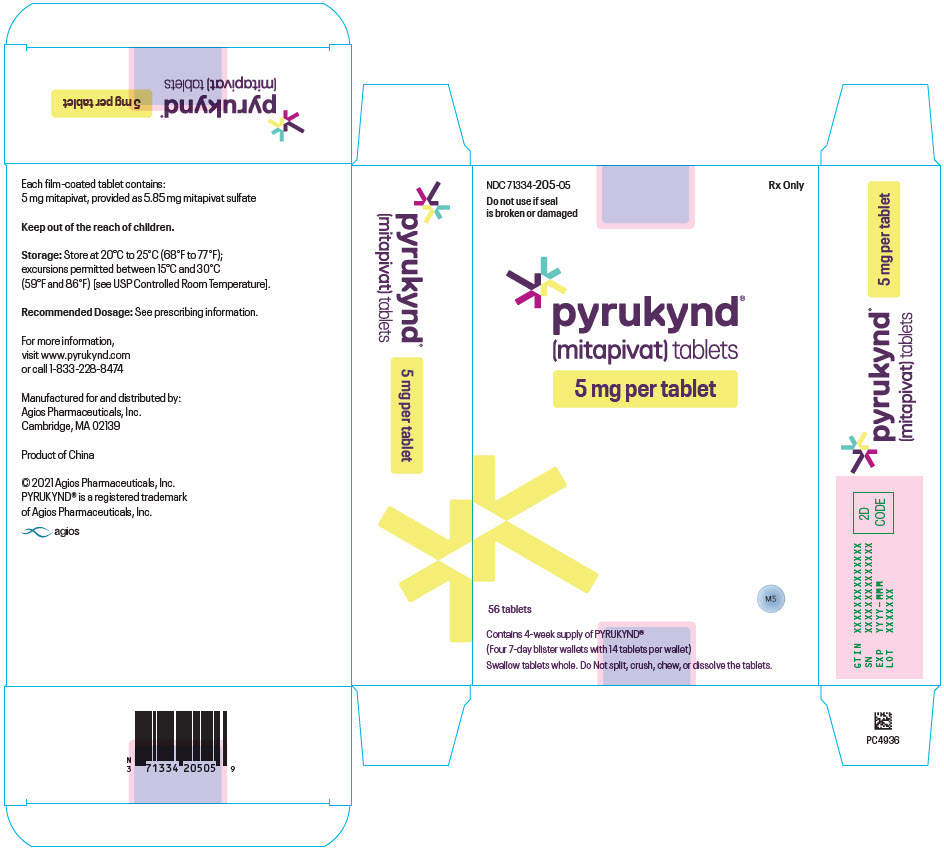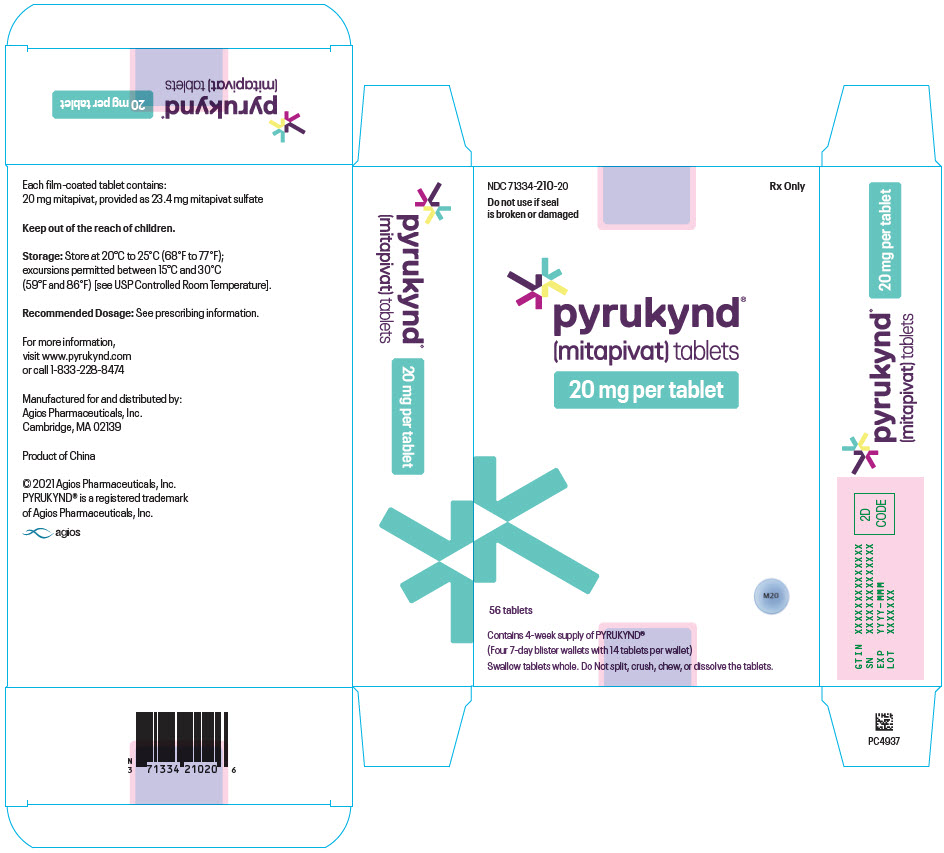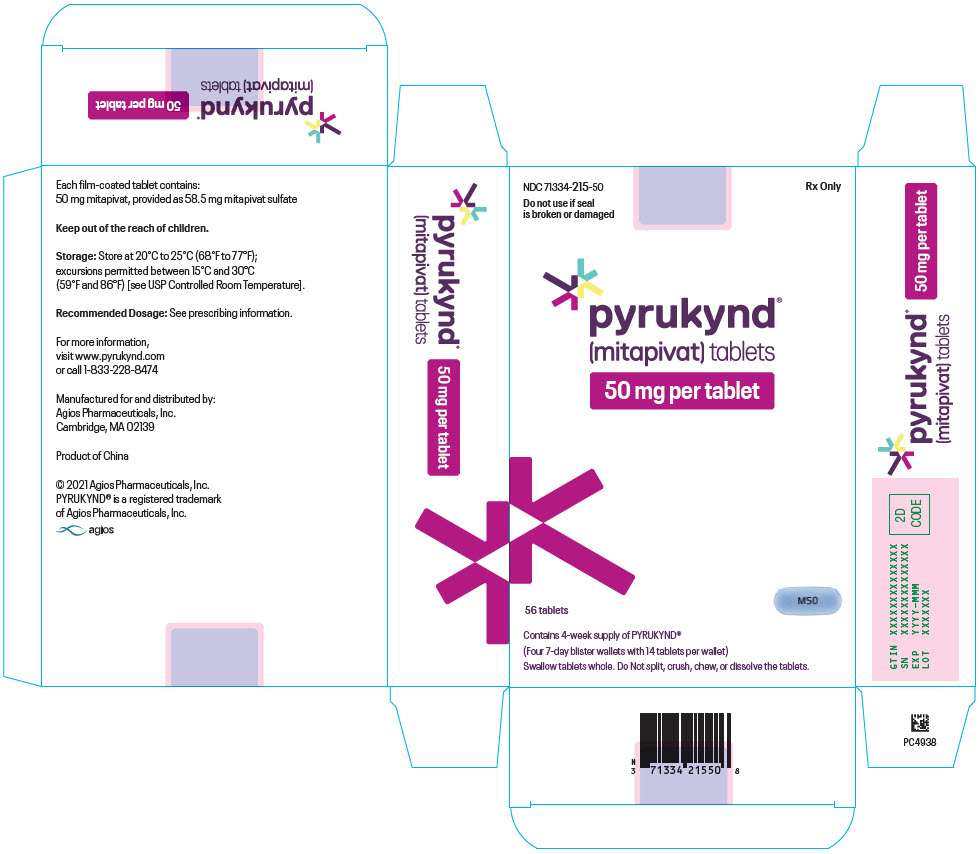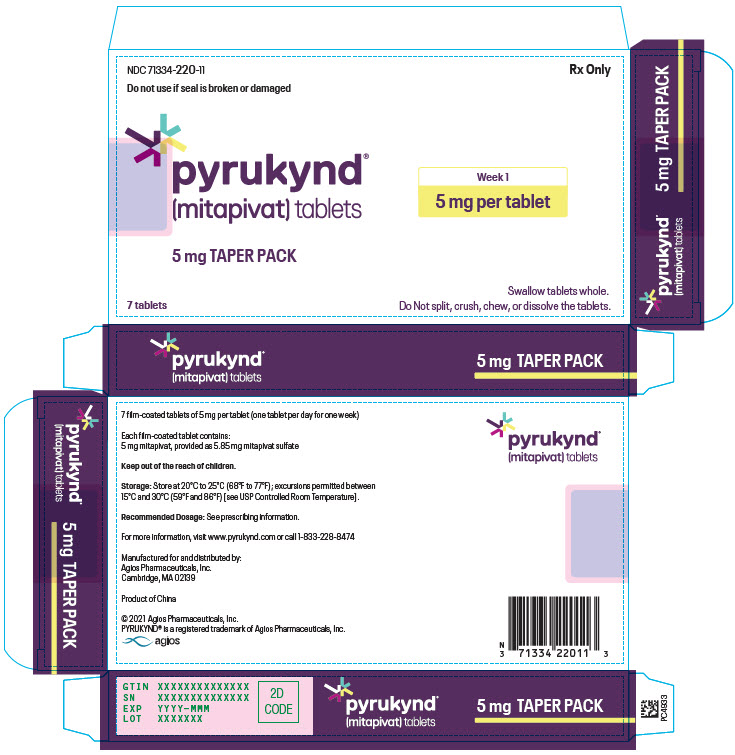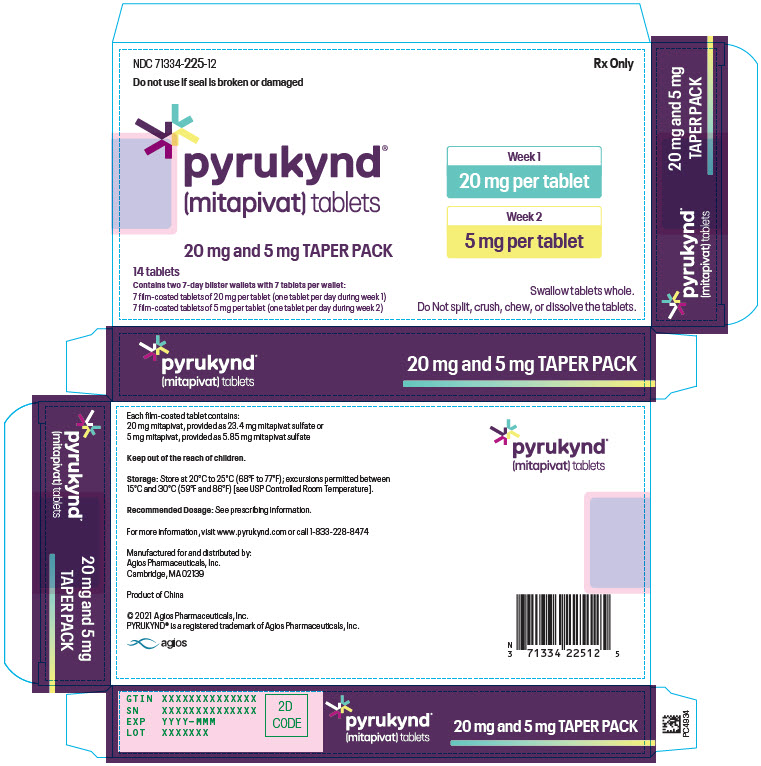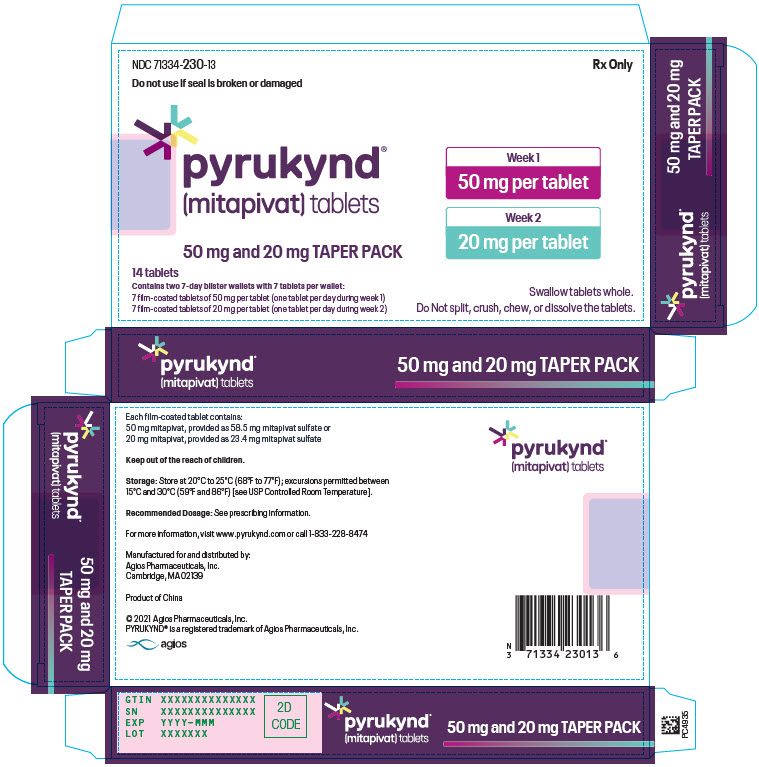 DRUG LABEL: PYRUKYND
NDC: 71334-205 | Form: TABLET, FILM COATED
Manufacturer: Agios Pharmaceuticals, Inc.
Category: prescription | Type: HUMAN PRESCRIPTION DRUG LABEL
Date: 20251230

ACTIVE INGREDIENTS: MITAPIVAT 5 mg/1 1
INACTIVE INGREDIENTS: CROSCARMELLOSE SODIUM; MANNITOL; MICROCRYSTALLINE CELLULOSE; SODIUM STEARYL FUMARATE; FD&C BLUE NO. 2; HYPROMELLOSE, UNSPECIFIED; LACTOSE MONOHYDRATE; TITANIUM DIOXIDE; TRIACETIN

HIGHLIGHTS OF PRESCRIBING INFORMATION

These highlights do not include all the information needed to use PYRUKYND safely and effectively. See full prescribing information for PYRUKYND.
PYRUKYND® (mitapivat) tablets, for oral use
Initial U.S. Approval: 2022

RECENT MAJOR CHANGES

Warnings and Precautions, Hepatocellular Injury in Another Condition (5.2) 01/2025

1 INDICATIONS AND USAGE

PYRUKYND is a pyruvate kinase activator indicated for the treatment of hemolytic anemia in adults with pyruvate kinase (PK) deficiency. (1)

2 DOSAGE AND ADMINISTRATION

- Starting dosage: 5 mg orally twice daily with or without food. (2.1)
- See Full Prescribing Information for dose titration and taper schedule. (2.1, 2.3)
- The tablet should be swallowed whole. (2.1)

3 DOSAGE FORMS AND STRENGTHS

Tablets: 5 mg, 20 mg, and 50 mg. (3)

4 CONTRAINDICATIONS

None (4)

5 WARNINGS AND PRECAUTIONS

- Acute Hemolysis: Avoid abrupt interruption or abrupt discontinuation of PYRUKYND to minimize the risk of acute hemolysis. A gradual reduction in dosing rather than abrupt cessation is recommended when possible. (5.1)
- Hepatocellular Injury in Another Condition: Obtain liver tests prior to the initiation of PYRUKYND and monthly thereafter for the first 6 months and as clinically indicated. Interrupt PYRUKYND if clinically significant increases in liver tests are observed or alanine aminotransferase is >5 times the upper limit of normal (ULN). Discontinue PYRUKYND if hepatic injury due to PYRUKYND is suspected. (5.2)

6 ADVERSE REACTIONS

The most common adverse reactions including laboratory abnormalities (≥ 10%) in patients with PK deficiency were estrone decreased (males), increased urate, back pain, estradiol decreased (males), and arthralgia. (6.1)

To report SUSPECTED ADVERSE REACTIONS, contact Agios Pharmaceuticals at 1-833-228-8474 or FDA at 1-800-FDA-1088 or www.fda.gov/medwatch.

7 DRUG INTERACTIONS

- Strong CYP3A Inhibitors and Inducers: Avoid concomitant use. (7.1)
- Moderate CYP3A Inhibitors: Do not titrate PYRUKYND beyond 20 mg twice daily. (7.1)
- Moderate CYP3A Inducers: Consider alternatives that are not moderate inducers. If there are no alternatives, adjust PYRUKYND dosage. (7.1)
- Sensitive CYP3A, CYP2B6, CYP2C substrates including hormonal contraceptives: Avoid concomitant use with substrates that have narrow therapeutic index. (7.2)
- UGT1A1 Substrates: Avoid concomitant use with substrates that have narrow therapeutic index. (7.2)
- P-gp Substrates: Avoid concomitant use with substrates that have narrow therapeutic index. (7.2)

8 USE IN SPECIFIC POPULATIONS

Hepatic Impairment: Avoid use of PYRUKYND in patients with moderate or severe hepatic impairment. (8.6)

FULL PRESCRIBING INFORMATION

RECENT MAJOR CHANGES

Warnings and Precautions, Hepatocellular Injury in Another Condition (5.2) 01/2025

1 INDICATIONS AND USAGE

PYRUKYND is indicated for the treatment of hemolytic anemia in adults with pyruvate kinase (PK) deficiency.

2 DOSAGE AND ADMINISTRATION

PYRUKYND is taken orally with or without food. The tablets should be swallowed whole. Do not split, crush, chew, or dissolve the tablets.

2.1 Recommended Dose

PYRUKYND is taken with or without food and swallowed whole. Do not split, crush, chew, or dissolve the tablets.

The starting dosage for PYRUKYND is 5 mg orally twice daily. To gradually increase hemoglobin (Hb), titrate PYRUKYND from 5 mg twice daily to 20 mg twice daily, and then to the maximum recommended dose of 50 mg twice daily, with these dose increases occurring every 4 weeks (see Table 1). Assess Hb and transfusion requirement before increasing to the next dose level, as some patients may reach and maintain normal Hb at 5 mg twice daily or 20 mg twice daily.

Discontinue PYRUKYND if no benefit has been observed by 24 weeks, based on the hemoglobin and hemolysis laboratory results and transfusion requirements.

Table 1: Dose Titration Schedule
Duration | Dosage
Week 1 through Week 4 | 5 mg twice daily
Week 5 through Week 8 | If Hb is below normal range or patient has required a transfusion within the last 8 weeks:; - Increase to 20 mg twice daily and maintain for 4 weeks. If Hb is within normal range and patient has not required a transfusion within the last 8 weeks: - Maintain 5 mg twice daily.
Week 9 through Week 12 | If Hb is below normal range or patient has required a transfusion within the last 8 weeks:; - Increase to 50 mg twice daily and maintain thereafter. If Hb is within normal range and patient has not required a transfusion within the last 8 weeks: - Maintain current dose (5 mg twice daily or 20 mg twice daily).
Maintenance | If Hb decreases, consider up-titration to the maximum of 50 mg twice daily as per the above schedule.

2.2 Missed Dose

If a dose of PYRUKYND is missed by 4 hours or less, administer the dose as soon as possible. If a dose of PYRUKYND is missed by more than 4 hours, do not administer a replacement dose, and wait until the next scheduled dose. Subsequently, return to the normal dosing schedule.

2.3 Interruption or Discontinuation

To reduce the risk of acute hemolysis, avoid abrupt interruption or abrupt discontinuation of PYRUKYND when possible [see Warnings and Precautions (5.1)]. Taper the dose to gradually discontinue the medication (see Table 2). Monitor patients for signs of acute hemolysis and worsening of anemia.

Table 2 Dose Taper Schedule
Current Dose | Dose Taper Schedule
Current Dose | Day 1-7 | Day 8-14 | Day 15
5 mg twice daily | 5 mg once daily | Discontinue | N/A
20 mg twice daily | 20 mg once daily | 5 mg once daily | Discontinue
50 mg twice daily | 50 mg once daily | 20 mg once daily | Discontinue
Abbreviations: N/A = not applicable.

2.4 Recommended Dosage for Drug Interactions

Strong CYP3A Inhibitors

Avoid co-administration of strong CYP3A inhibitors with PYRUKYND [see Drug Interactions (7.1) and Clinical Pharmacology (12.3)].

Moderate CYP3A Inhibitors

Monitor Hb and for increased risks of adverse reactions from PYRUKYND. When used with a moderate CYP3A inhibitor, do not titrate PYRUKYND beyond 20 mg twice daily [see Drug Interactions (7.1) and Clinical Pharmacology (12.3)].

Strong CYP3A Inducers

Avoid co-administration of strong CYP3A inducers with PYRUKYND [see Drug Interactions (7.1) and Clinical Pharmacology (12.3)].

Moderate CYP3A Inducers

Consider alternative therapies that are not moderate CYP3A inducers during treatment with PYRUKYND. If there are no alternative therapies, monitor Hb and titrate beyond the 50 mg twice daily dose, if necessary, but do not exceed a maximum recommended dose of 100 mg twice daily [see Drug Interactions (7.1) and Clinical Pharmacology (12.3)].

2.5 Dose Modifications for Adverse Reactions and Hemoglobin Levels Above Normal

If a dose reduction is required because of an adverse reaction or tolerability, or for Hb above normal, the dose may be reduced to the next lower dose level, 20 mg twice daily or 5 mg twice daily.

If a patient needs to discontinue PYRUKYND, the dose taper schedule (Table 2) should be followed. In situations where the risk to the patient due to the adverse reaction or Hb above normal is greater than the risk of acute hemolysis due to sudden withdrawal of the drug, treatment may be stopped without taper and patients should be monitored for signs of acute hemolysis.

3 DOSAGE FORMS AND STRENGTHS

- 5 mg tablets: round, blue, film-coated tablets with "M5" printed on one side.
- 20 mg tablets: round, blue, film-coated tablets with "M20" printed on one side.
- 50 mg tablets: oblong, blue, film-coated tablets with "M50" printed on one side.

4 CONTRAINDICATIONS

None

5 WARNINGS AND PRECAUTIONS

5.1 Acute Hemolysis with Abrupt Treatment Interruption

Acute hemolysis with subsequent anemia has been observed following abrupt interruption or discontinuation of PYRUKYND in a dose-ranging study. Avoid abruptly discontinuing PYRUKYND. Gradually taper the dose of PYRUKYND to discontinue treatment if possible [see Dosage and Administration (2.3, 2.6)]. When discontinuing treatment, monitor patients for signs of acute hemolysis and anemia including jaundice, scleral icterus, dark urine, dizziness, confusion, fatigue, or shortness of breath.

5.2 Hepatocellular Injury in Another Condition

In patients with another condition treated with mitapivat at a higher dose than that recommended for patients with PK deficiency, liver injury has been observed. These events were characterized by a time to onset within the first 6 months of treatment with peak elevations of alanine aminotransferase of >5×ULN with or without jaundice. All patients discontinued treatment with PYRUKYND, and these events improved upon treatment discontinuation.

Obtain liver tests prior to the initiation of PYRUKYND and monthly thereafter for the first 6 months and as clinically indicated. Interrupt PYRUKYND if clinically significant increases in liver tests are observed or alanine aminotransferase is >5 times the upper limit of normal (ULN). Discontinue PYRUKYND if hepatic injury due to PYRUKYND is suspected.

6 ADVERSE REACTIONS

The following clinically significant adverse reaction is described elsewhere in labeling:

- Acute Hemolysis with Abrupt Treatment Discontinuation [see Warnings and Precautions (5.1)].
- Hepatocellular Injury in Another Condition [see Warnings and Precautions (5.2)].

6.1 Clinical Trial Experience

Because clinical trials are conducted under widely varying conditions, adverse reaction rates observed in the clinical trials of a drug cannot be directly compared to rates in the clinical trials of another drug and may not reflect the rates observed in practice.

A total of 155 patients received PYRUKYND, 79% of whom were exposed for longer than 24 weeks. PYRUKYND was administered up to 50 mg orally twice daily in 67 patients with PK deficiency in the ACTIVATE trial (N=40) and the ACTIVATE-T trial (N=27) [see Clinical Studies (14)].

ACTIVATE Trial

In the ACTIVATE trial patients with PK deficiency who were not regularly transfused received PYRUKYND in incremental doses up to 50 mg twice daily (N=40) or placebo (N=39).

Serious adverse reactions occurred in 10% of patients receiving PYRUKYND in the ACTIVATE Trial, including atrial fibrillation, gastroenteritis, rib fracture, and musculoskeletal pain, which each occurred in 1 patient.

In the ACTIVATE trial, the most common adverse reactions including laboratory abnormalities (≥10%) in patients with PK deficiency were estrone decreased (males), increased urate, back pain, estradiol decreased (males), and arthralgia.

Table 3 summarizes the adverse reactions in the ACTIVATE trial.

Table 3: Adverse Reactions (≥ 5%) in Patients Receiving PYRUKYND in ACTIVATE
 | PYRUKYND; (N=40) |  | Placebo; (N=39)
Adverse Reaction | All Grades; (%) | Grade ≥3; (%) | All Grades; (%) | Grade ≥3; (%)
Back paina | 15% | 0 | 8% | 0
Arthralgiab | 10% | 0 | 5% | 0
Hypertriglyceridemiac | 8% | 5% | 3% | 0
Gastroenteritis | 8% | 3% | 0 | 0
Hot flushd | 8% | 0 | 0 | 0
Oropharyngeal pain | 8% | 0 | 5% | 0
Hypertension | 5% | 5% | 0 | 0
Arrhythmiae | 5% | 0 | 0 | 0
Breast discomfort | 5% | 0 | 0 | 0
Constipation | 5% | 0 | 0 | 0
Dry mouthf | 5% | 0 | 0 | 0
Paresthesia | 5% | 0 | 0 | 0
Grades: Per the CTCAE definition.
Grouped Term Definitions
a Includes back pain, sciatica, and flank pain.
b Includes arthralgia and joint swelling.
c Includes hypertriglyceridemia and blood triglycerides increased.
d Includes hot flush and flushing.
e Includes arrhythmia, tachycardia, heart rate increased and atrial fibrillation.
f Includes dry mouth and dry lip.

Laboratory abnormalities of PYRUKYND included increased urate (15%).

Variations in Reproductive Hormones

In ACTIVATE, increases in serum testosterone and decreases in serum estrone and estradiol were observed in men receiving PYRUKYND (Table 4). These changes in hormones persisted throughout the study period. In patients who discontinued PYRUKYND and had follow-up hormone measurements, the hormone changes returned close to the baseline levels 28 days after discontinuing PYRUKYND. In female patients, sex hormone analysis was limited due to physiologic variations in hormones during the menstrual cycle and the use of hormonal contraceptives.

Table 4: Laboratory Abnormalities in Reproductive Hormones in Men Receiving PYRUKYND
 | ACTIVATE
Parameter | PYRUKYND (16 males) n (%) | Placebo (15 males)n (%)
Reproductive hormone analysesa
Estrone decreased (males) Estradiol decreased (males) Blood testosterone increased (males) | 9 (56.3) 2 (12.5) 1 (6.3) | 0 1 (6.7) 1 (6.7)
a Decreases in estrone and estradiol to below the lower limit of the reference range and increases in testosterone to above the upper limit of the reference range where baseline was within normal limits.

ACTIVATE-T Trial

The adverse reactions reported in the population of patients who were regularly transfused (ACTIVATE-T) were consistent with that seen in ACTIVATE.

7 DRUG INTERACTIONS

7.1 Effect of Other Drugs on PYRUKYND

Strong CYP3A Inhibitors
Clinical Impact | - Co-administration of PYRUKYND with strong CYP3A inhibitors increased mitapivat plasma concentrations [see Clinical Pharmacology (12.3)]. - Increased mitapivat plasma concentrations may increase the risks of adverse reactions of PYRUKYND.
Prevention or Management | - Avoid co-administration of strong CYP3A inhibitors with PYRUKYND [see Dosage and Administration (2.5)].
Moderate CYP3A Inhibitors
Clinical Impact | - Co-administration of PYRUKYND with moderate CYP3A inhibitors will increase mitapivat plasma concentrations [see Clinical Pharmacology (12.3)].
Prevention or Management | - Monitor Hb and for increased risks of adverse reactions with PYRUKYND. - Do not titrate PYRUKYND beyond 20 mg twice daily [see Dosage and Administration (2.5)].
Strong CYP3A Inducers
Clinical Impact | - Co-administration of PYRUKYND with strong CYP3A inducers decreased mitapivat plasma concentrations [see Clinical Pharmacology (12.3)]. - Decreased mitapivat plasma concentrations will reduce the efficacy of PYRUKYND.
Prevention or Management | - Avoid co-administration of strong CYP3A inducers with PYRUKYND [see Dosage and Administration (2.5)].
Moderate CYP3A Inducers
Clinical Impact | - Co-administration of PYRUKYND with moderate CYP3A inducers will decrease mitapivat plasma concentrations [see Clinical Pharmacology (12.3)].
Prevention or Management | - Consider alternative therapies that are not moderate CYP3A inducers during treatment with PYRUKYND. If there are no alternative therapies, monitor Hb and titrate beyond 50 mg twice daily, if necessary, but do not exceed a maximum recommended dose of 100 mg twice daily [see Dosage and Administration (2.5)].

7.2 Effect of PYRUKYND on Other Drugs

CYP3A Substrates
Clinical Impact | - PYRUKYND induces CYP3A. Co-administration of PYRUKYND will decrease systemic concentrations of drugs that are sensitive CYP3A substrates, including hormonal contraceptives (e.g., ethinyl estradiol) [see Clinical Pharmacology (12.3)].
Prevention or Management | - Monitor patients for loss of therapeutic effect of sensitive CYP3A substrates with narrow therapeutic index when co- administered with PYRUKYND. - Advise patients using hormonal contraceptives to use an alternative non-hormonal contraceptive method or add a barrier method of contraception during treatment with PYRUKYND.
CYP2B6 and CYP2C Substrates
Clinical Impact | - PYRUKYND induces CYP2B6, CYP2C8, CYP2C9, and CYP2C19 enzymes in vitro, and may decrease systemic concentrations of drugs that are sensitive substrates of these enzymes [see Clinical Pharmacology (12.3)].
Prevention or Management | - Monitor patients for loss of therapeutic effect of sensitive substrates of these enzymes with narrow therapeutic index when co-administered with PYRUKYND.
UGT1A1 Substrates
Clinical Impact | - PYRUKYND induces UGT1A1 in vitro and may decrease systemic concentrations of drugs that are UGT1A1 substrates [see Clinical Pharmacology (12.3)].
Prevention or Management | - Monitor patients for loss of therapeutic effect of UGT1A1 substrates with narrow therapeutic index when co-administered with PYRUKYND.
P-gp Substrates
Clinical Impact | - PYRUKYND inhibits the P-gp transporter in vitro and may increase systemic concentrations of drugs that are P-gp substrates [see Clinical Pharmacology (12.3)].
Prevention or Management | - Monitor patients for adverse reactions of P-gp substrates with narrow therapeutic index when co-administered with PYRUKYND.

8 USE IN SPECIFIC POPULATIONS

8.1 Pregnancy

Risk Summary

Available data from clinical trials of PYRUKYND are insufficient to evaluate for a drug- associated risk of major birth defects, miscarriage or other adverse maternal or fetal outcomes.

In animal reproduction studies, mitapivat orally administered twice daily to pregnant rats and rabbits during organogenesis was not teratogenic at doses up to 13 and 3 times the maximum recommended human dose (MRHD) of 50 mg twice daily, respectively. Mitapivat administered orally to pregnant rats twice daily during organogenesis through lactation did not result in adverse developmental effects at doses up to 13 times the MRHD (see Data).

The estimated background risk of major birth defects for the indicated population is unknown. Estimated frequencies for other important background risks in the population are as follows: miscarriage 18%, growth retardation 24%, preterm birth 56%. All pregnancies have a background risk of birth defect, loss, or other adverse outcomes. In the U.S. general population, the estimated background risk of major birth defects and miscarriage in clinically recognized pregnancies is 2% to 4% and 15% to 20%, respectively.

Clinical Considerations

Disease-Associated Maternal Risk

Untreated PK deficiency in pregnant women may precipitate acute hemolysis, pre-term labor, miscarriage and severe anemia requiring frequent transfusion. Additionally, preeclampsia and severe hypertension have been reported.

Data

Animal Data

In an embryo-fetal development study in rats, mitapivat was administered at doses of 5, 10, 25, and 100 mg/kg twice daily by oral gavage during the period of organogenesis (gestation days 6 to 17). There was a statistically significant 14% decrease in maternal net body weight gain at the high dose with associated decrease in food consumption. Enlarged or fused placenta and/or a distended amniotic sac, an increase in post-implantation loss (early and late resorptions), a decrease in the mean number of viable fetuses, lower mean fetal weights, and external, visceral, and skeletal malformations were observed at the high dose (100 mg/kg twice daily, 63 times the MRHD, based on area under the plasma drug concentration-time curve [AUC]). No maternal or embryo-fetal toxicity was observed up to 25 mg/kg twice daily (13 times the MRHD, based on AUC).

In an embryo-fetal development study in rabbits, mitapivat was administered at doses of 12.5, 30, and 62.5 mg/kg twice daily by oral gavage during the period of organogenesis (gestation days 7 to 20). Lower fetal weight was observed at 62.5 mg/kg twice daily (3 times MRHD, based on AUC) and correlated with reduced maternal body weight gain. No effects on fetal morphology were observed.

In a pre- and post-natal development study in rats, mitapivat was administered at doses of 5, 10, 25, and 100 mg/kg twice daily by oral gavage during the period of organogenesis and continuing to weaning (gestation day 7 to lactation day 20). Dystocia was observed at ≥25 mg/kg twice daily (≥13x MRHD, based on AUC). At 100 mg/kg twice daily (63x MRHD, based on AUC) decreased maternal body weight gain, prolonged parturition, and dystocia occurred and resulted in maternal mortality, complete litter loss, decreased pup viability and decreased pup body weight. No adverse effects on pup growth and development, and reproductive performance were observed up to 50 mg/kg (13 times the MRHD, based on AUC).

8.2 Lactation

Risk Summary

There are no data on the presence of PYRUKYND or its metabolites in human or animal milk, the effects on the breastfed child, or the effects on milk production. The developmental and health benefits of breastfeeding should be considered along with the mother’s clinical need for PYRUKYND and any potential adverse effects on the breastfed child from PYRUKYND or from the underlying maternal condition.

8.4 Pediatric Use

Safety and effectiveness in pediatric patients have not been established.

8.5 Geriatric Use

Clinical studies of PYRUKYND did not include sufficient numbers of subjects aged 65 years and over to determine whether they respond differently from younger subjects.

8.6 Renal Impairment

Mitapivat undergoes extensive hepatic metabolism. Moderate and severe hepatic impairment is expected to increase the systemic exposure of mitapivat. Avoid use of PYRUKYND in patients with moderate and severe hepatic impairment [see Dosage and Administration (2.4), Warnings and Precautions (5.2), and Clinical Pharmacology (12.3)].

11 DESCRIPTION

The active ingredient of PYRUKYND is mitapivat, a pyruvate kinase activator, present as mitapivat sulfate. The chemical name of mitapivat sulfate is 8-quinolinesulfonamide, N-[4-[[4- (cyclopropylmethyl)-1-piperazinyl]carbonyl]phenyl]-, sulfate, hydrate (2:1:3). The chemical structure of mitapivat sulfate is:

The molecular formula is (C24H26N4SO3)2 • H2SO4 • 3H2O, and the molecular weight is 1053.23 for mitapivat sulfate. Mitapivat sulfate is a white to off-white solid and is slightly soluble in water.

PYRUKYND is available as 5 mg, 20 mg, and 50 mg tablets for oral administration. Each tablet contains 5 mg, 20 mg, or 50 mg mitapivat free base, provided as 5.85 mg, 23.4 mg, or 58.5 mg, respectively, of the sulfate hydrate salt, and the following inactive ingredients: croscarmellose sodium, mannitol, microcrystalline cellulose, and sodium stearyl fumarate. The tablet film coating contains the inactive ingredients FD&C Blue No. 2, hypromellose, lactose monohydrate, titanium dioxide, and triacetin. The tablets are imprinted with black ink containing the inactive ingredients ammonium hydroxide, ferrosoferric oxide, isopropyl alcohol, n-butyl alcohol, propylene glycol, and shellac glaze.

12 CLINICAL PHARMACOLOGY

12.1 Mechanism of Action

Mitapivat is a pyruvate kinase activator that acts by allosterically binding to the pyruvate kinase tetramer and increasing pyruvate kinase (PK) activity. The red blood cell (RBC) form of pyruvate kinase (PK-R) is mutated in PK deficiency, which leads to reduced adenosine triphosphate (ATP), shortened RBC lifespan, and chronic hemolysis.

12.2 Pharmacodynamics

Mitapivat decreases 2,3 diphosphoglycerate (2,3-DPG) and increases ATP in healthy volunteers.

Cardiac Electrophysiology

At a dose 6 times the maximum recommended dose, mitapivat did not prolong the QT interval to any clinically relevant extent.

12.3 Pharmacokinetics

Mitapivat exposure increased in an approximately dose proportional manner over the clinically relevant dose range of 5 mg to 50 mg twice daily.

The population pharmacokinetic model simulated Cmax, Ctrough, AUC0-12 and accumulation ratio of mitapivat at recommended dosages are listed in the table below.

Table 5: Steady State Mitapivat Exposure at Recommended Dosagesa
Mitapivat Dosage | Cmax (ng/mL) | Ctrough (ng/mL) | AUC 0-12 (ng*h/mL) | Accumulation Ratio
5 mg twice daily | 101.2 (17%) | 10.1 (74%) | 450.4 (28%) | 1.2
20 mg twice daily | 389.9 (18%) | 32.3 (77%) | 1623.8 (28%) | 1.1
50 mg twice daily | 935.2 (18%) | 62.1 (80%) | 3591.4 (28%) | 1.0
a Pharmacokinetic parameters are presented as geometric mean (CV%). The simulations were performed until 100 days after first dose. The interval of the last 12 hours was selected for steady state PK parameters calculation.
Residual error was not included during simulation.

Absorption

Median tmax values at steady state were 0.5 to 1.0 hour post-dose across the dose range of 5 mg to 50 mg twice daily.

The absolute bioavailability after a single dose was approximately 73%.

Effect of Food

Following administration of a single dose of PYRUKYND in healthy subjects, a high-fat meal (approximately 900 to 1,000 total calories, with 500 to 600 calories from fat, 250 calories from carbohydrate, and 150 calories from protein) did not change the exposure (AUCinf) of mitapivat, but reduced the rate of mitapivat absorption, with a 42% reduction in Cmax and a delay in tmax of 2.3 hours when compared to dosing under fasted conditions.

Distribution

Mitapivat is highly protein bound (97.7%) in plasma with low RBC distribution (RBC-to-plasma ratio of 0.37). The mean volume of distribution at steady state (Vss) was 42.5 L.

Elimination

The mean effective half-life (t1/2) of mitapivat ranged from 3 to 5 hours following multiple dose administrations of 5 mg twice daily to 20 mg twice daily in patients with PK deficiency.

Population pharmacokinetics derived median CL/F at steady state was 11.5, 12.7, and 14.4 L/h for the 5 mg twice daily, 20 mg twice daily, and 50 mg twice daily regimens, respectively.

Metabolism

In vitro studies showed that mitapivat is primarily metabolized by CYP3A4. Following a single oral dose of 120 mg of radiolabeled mitapivat to healthy subjects, unchanged mitapivat was the major circulating component.

Excretion

After a single oral administration of radiolabeled mitapivat to healthy subjects, the total recovery of administered radioactive dose was 89.2%, with 49.6% in the urine (2.6% unchanged) and 39.6% in the feces (<1% unchanged).

Specific Populations

No clinically meaningful effects on the pharmacokinetics of mitapivat were observed based on age, sex, race, or body weight.

Pediatric Population

The pharmacokinetics of mitapivat in children and adolescents (˂18 years old) have not been studied.

Hepatic Impairment

Mitapivat undergoes extensive hepatic metabolism. Moderate and severe hepatic impairment is expected to increase the systemic exposure of mitapivat. The pharmacokinetics of mitapivat in patients with hepatic impairment have not been studied.

Renal Impairment

The effects of renal impairment on mitapivat pharmacokinetics were assessed with population pharmacokinetic analyses. Steady state AUC of mitapivat in patients with eGFR 60 to <90 mL/min/1.73 m^2 was not significantly different compared to patients with eGFR ≥90 mL/min/1.73 m^2. There are limited data available in patients with eGFR 30 to <60 mL/min/1.73 m^2 and no data available in patients with eGFR <30 mL/min/1.73 m^2.

Drug Interaction Studies

Clinical Studies and Model-Based Approaches

Effect of Strong CYP3A Inhibitors on PYRUKYND

Itraconazole (a strong CYP3A inhibitor) increased mitapivat AUCinf and Cmax by 4.9-fold and 1.7-fold, respectively, following a single PYRUKYND dose of 20 mg. Itraconazole increased mitapivat AUC0-12 and Cmax by 3.6-fold and 2.2-fold, respectively, following PYRUKYND 50 mg twice daily. Ketoconazole (a strong CYP3A inhibitor) increased mitapivat AUC0-12 and Cmax by approximately 3.9-fold and 2.4-fold, respectively, following PYRUKYND doses of 5, 20 or 50 mg twice daily.

Effect of Moderate CYP3A Inhibitors on PYRUKYND

Fluconazole (a moderate CYP3A inhibitor) increased mitapivat AUC0-12 and Cmax by approximately 2.6-fold and 1.6-fold, respectively, following PYRUKYND doses of 5, 20 or 50 mg twice daily.

Effect of Strong CYP3A Inducers on PYRUKYND

Rifampin (a strong CYP3A inducer) decreased mitapivat AUCinf and Cmax by 91% and 77%, respectively, following a single PYRUKYND dose of 50 mg. Rifampin decreased mitapivat AUC0-12 and Cmax by approximately 95% and 85%, respectively, following PYRUKYND doses of 5, 20 or 50 mg twice daily.

Effect of Moderate CYP3A Inducers on PYRUKYND

Efavirenz (a moderate CYP3A4 inducer) decreased mitapivat AUC0-12 and Cmax by approximately 60% and 30%, respectively, following PYRUKYND doses of 5 or 20 mg twice daily. Efavirenz decreased mitapivat AUC0-12 and Cmax by 55% and 24%, respectively, following PYRUKYND doses of 50 mg twice daily.

Effect of PYRUKYND on CYP3A substrates

Midazolam (a CYP3A substrate) AUCinf and Cmax decreased by 21% and 19%, respectively, following co-administration of midazolam with PYRUKYND 5 mg twice daily. Midazolam AUCinf and Cmax decreased by 43% and 39%, respectively, following co-administration with PYRUKYND 20 mg twice daily, and 57% and 52%, respectively, with PYRUKYND 50 mg twice daily.

Effect of PYRUKYND on P-gp Substrates

Co-administration of PYRUKYND with drugs that are substrates of P-gp may result in a clinically relevant increase in plasma concentrations of these substrates.

In vitro Studies

CYP450 and UGT Enzymes

Mitapivat induces CYP2B6, CYP2C8, CYP2C9, CYP2C19, and UGT1A1.

Drug Transporter Systems

Mitapivat is a substrate and an inhibitor of P-gp.

13 NONCLINICAL TOXICOLOGY

13.1 Carcinogenesis, Mutagenesis, Impairment of Fertility

Carcinogenesis

Mitapivat was not carcinogenic in transgenic rasH2 mice up to the highest doses tested at 500 mg/kg/day in males and at 250 mg/kg/day in females when given orally for 26 weeks.

Mitapivat was not carcinogenic in rats when given orally up to 300 mg/kg/day in males and 200 mg/kg/day in females, at systemic exposures 47 times and >100 times the MRHD, respectively, based on AUC.

Mutagenesis

Mitapivat was not mutagenic in an in vitro bacterial reverse mutation (Ames) assay. Mitapivat was not clastogenic in an in vitro human lymphocyte micronucleus assay or in an in vivo rat bone marrow micronucleus assay.

Fertility

In a fertility and early embryonic development study, oral administration of mitapivat twice daily in male rats prior to and during mating at doses up to 300 mg/kg/day, which represents 45 times the MRHD of 50 mg twice daily, based on AUC, did not result in adverse effects on fertility or reproductive function. In female rats, twice daily oral administration of mitapivat prior to mating and continuing through organogenesis, at doses up to 200 mg/kg/day, which represents 48 times the MRHD of 50 mg twice daily, based on AUC, did not result in adverse effects on fertility or reproductive function.

14 CLINICAL STUDIES

Patients with PK Deficiency

Patients Not Regularly Transfused

The efficacy of PYRUKYND was evaluated in ACTIVATE, a multinational, randomized, double-blind, placebo-controlled clinical study (NCT03548220) of 80 adults with PK deficiency who were not regularly transfused, defined as having had no more than 4 transfusions in the 52- week period prior to treatment and no transfusions in the 3-month period prior to treatment.

Patients were included if they had documented presence of at least 2 variant alleles in the pyruvate kinase liver and red blood cell (PKLR) gene, of which at least 1 was a missense variant, and Hb less than or equal to 10 g/dL. Patients who were homozygous for the c.1436G>A (p.R479H) variant or had 2 non-missense variants (without the presence of another missense variant) in the PKLR gene were excluded because these patients did not achieve Hb response (change from baseline in Hb ≥1.5 g/dL at >50% assessments) in the dose-ranging study.

Randomization was stratified by average screening Hb (<8.5 vs ≥8.5 g/dL) and PKLR gene variant category (missense/missense vs. missense/non-missense).

Among the 80 patients with PK deficiency, 40 patients were randomized to PYRUKYND. Following a period of dose titration up to 50 mg twice daily, patients continued a fixed dose of PYRUKYND for 12 weeks. Eighty-eight percent of patients were maintained on 50 mg twice daily.

The median duration of treatment with PYRUKYND was 24.1 weeks (range 23.6 to 27.4 weeks). Overall, 30 (75%) patients were exposed to PYRUKYND for >24 weeks and <28 weeks. Among the 80 randomized patients, the median age was 33 years (range 18 to 78) and 40% were male; race was reported in 88% of patients: 75% were White, 10% Asian, 1.3% Native Hawaiian/Other Pacific Islander and 1.3% were other races. The median baseline hemoglobin was 8.5 g/dL (range: 6.4 to 10.2 g/dL). There were 55 patients (69%) with the missense/missense PKLR gene variant category, and 25 patients (31%) with the missense/non-missense PKLR gene variant category. There were 58 patients (73%) who had a history of splenectomy. Complications and comorbidities associated with PK deficiency included iron overload with a median baseline ferritin of 479 ng/mL (range: 21 to 5890 ng/mL), chelation therapy use in the year before the first dose of study treatment in 15 patients (19%), decreased bone mineral density in 64 patients (80%) who had a baseline femoral neck T-score or lumbar spine T-score <-1.0, and history of cholecystectomy in 58 patients (73%).

Efficacy was based upon Hb response, defined as a ≥1.5 g/dL increase in Hb from baseline sustained at 2 or more scheduled assessments (Weeks 16, 20, and 24) during the fixed dose period without transfusions. The efficacy results, including changes in markers of hemolysis are shown in Table 6.

Table 6: Efficacy Results in Patients with PK Deficiency Who Were Not Regularly Transfused (ACTIVATE)
Endpoint | PYRUKYND N=40 | Placebo N=40 | Difference^1,^2 p-value
Hb Response, n (%) | 16 (40%) | 0 | 39 (24, 55) <0.0001
Hemoglobin (g/dL) Baseline Mean (SD) LS Mean Change (95% CI) | 8.6 (1.0) 1.7 (1.3, 2.1) | 8.5 (0.8) -0.1 (-0.6, 0.3) | 1.8 (1.2, 2.4) <0.0001
Indirect bilirubin (mg/dL) Baseline Mean (SD) LS Mean Change (95% CI) | 4.8 (3.6) -1.2 (-1.7, -0.7) | 5.2 (3.6) 0.3 (-0.2, 0.8) | -1.5 (-2.2, -0.9) <0.0001
Reticulocyte (fraction of 1) Baseline Mean (SD) LS Mean Change (95% CI) | 0.37 (0.24) -0.10 (-0.13, -0.07) | 0.40 (0.22) 0 (-0.02, 0.03) | -0.10 (-0.14, -0.06) <0.0001
LDH (U/L) Baseline Mean (SD) LS Mean Change (95% CI) | 348 (276) -92 (-124, -60) | 260 (140) -21 (-53, 11) | -71 (-116, -26) 0.003
Haptoglobin (mg/dL) Baseline Mean (SD) LS Mean Change (95% CI) | 8.2 (10.7) 16.9 (8.8, 25.1) | 8.3 (13.8) 1.2 (-7.0, 9.4) | 15.8 (4.3, 27.3) 0.008
CI: confidence interval, Hb: hemoglobin, LDH: lactate dehydrogenase, LS Mean Change: least square mean change from baseline, SD: standard deviation
^1 All results are statistically significant.
^2 For Hb response, the difference is adjusted for randomization stratification factors, which included average screening Hb (<8.5, ≥8.5 g/dL) and PKLR gene variant category (missense/missense, missense/non-missense). The two-sided p-value is based on the Mantel-Haenszel stratum weighted method adjusting for the randomization stratification factors.
For the endpoints of average change from baseline at Weeks 16, 20, and 24 for hemoglobin, indirect bilirubin, reticulocytes, LDH, and haptoglobin, the two-sided p-value is based on the mixed-effect model repeat measurement (MMRM) method, which included change from baseline as the dependent variable, baseline as a covariate, and treatment arm, visit, treatment-by-visit interaction, and the randomization stratification factors as fixed factors and subject as the random effect. All scheduled visits were included in the model.

In ACTIVATE, the LS Mean change from baseline with PYRUKYND compared to placebo was -0.4 (standard error [SE] 0.1) for jaundice (scale: 0-4), -1.1 (SE 0.4) for tiredness (scale: 0-10), and -0.3 (SE 0.3) for shortness of breath (scale: 0-10), assessed with the daily Pyruvate Kinase Deficiency Diary (PKDD) where lower scores represent less sign/symptom severity.

In ACTIVATE, the majority of PYRUKYND-treated patients experienced an increase in Hb, while the majority of patients in the placebo arm experienced a decrease in Hb as measured by average change from baseline at weeks 16, 20, and 24 (Figure 1).

a Approximately 99% of all randomized patients completed 24 weeks of treatment.

CI: confidence interval, Hb: hemoglobin, LS: least square

Fifteen of the 16 patients with a Hb response in ACTIVATE continued in a long-term extension study and were evaluable for maintenance of response. Thirteen maintained increases in Hb concentration from baseline above the response threshold of ≥1.5 g/dL at the last available Hb assessment without requiring any transfusions. The median duration of response for the 16 patients with Hb response was 6.9 months (range: 3.3, 18.4+).

Patients Who Were Regularly Transfused

The efficacy of PYRUKYND in patients with PK deficiency who were regularly transfused was evaluated in ACTIVATE-T, a multinational single-arm clinical trial (NCT03559699) of 27 adults with PK deficiency who had a minimum of 6 transfusion episodes in the 52-week period prior to informed consent. Patients were included if they had documented presence of at least 2 variant alleles in the PKLR gene, of which at least 1 was a missense variant. Patients who were homozygous for the c.1436G>A (p.R479H) variant or had 2 non-missense variants (without the presence of another missense variant) in the PKLR gene were excluded. Following a period of dose titration up to 50 mg twice daily, patients continued on a fixed dose of PYRUKYND for 24 weeks.

The median duration of treatment with PYRUKYND was 40.3 weeks (range 16.3 to 46.3 weeks). Overall, 20 (74%) patients were exposed to PYRUKYND for >40 weeks and <47 weeks. The median age was 36 years (range 18 to 68) and 26% were male; race was reported in 85% of patients: 74% were White and 11% Asian. The median baseline hemoglobin was 9.1 g/dL (range: 7.4 to 10.9 g/dL). Patients had a median of 9 transfusion episodes (range: 6 to 17 episodes) in the 52 weeks before the first dose of study treatment and a median of 7 red blood cell units transfused (range: 3 to 20 units) standardized to 24 weeks. There were 20 patients (74%) with the missense/missense PKLR gene variant category, and 7 patients (26%) with the missense/non-missense PKLR gene variant category. There were 21 patients (78%) who had a history of splenectomy. Patients had evidence of complications and comorbidities associated with PK deficiency including iron overload (median baseline ferritin was 1324 ug/L; range: 163 to 5357 ng/mL), chelation therapy use in the year before the first dose of study treatment in 24 patients (89%), decreased bone mineral density in 20 patients (74%) who had a baseline femoral neck T-score or lumbar spine T-score <-1.0, and history of cholecystectomy in 23 patients (85%).

Efficacy was based on transfusion reduction response and was defined as ≥33% reduction in the number of red blood cell (RBC) units transfused during the fixed dose period compared with the patient’s historical transfusion burden.

Efficacy results for patients with PK deficiency who were regularly transfused are presented in Table 7.

Table 7: Efficacy Results in Patients with PK Deficiency Who Were Regularly Transfused (ACTIVATE-T)
Endpoints | PYRUKYND N=27
Patients with Transfusion Reduction Response n (%) 95% CI | 9 (33) (17, 54)
Patients who were Transfusion Free n (%) 95% CI | 6 (22) (9, 42)
CI: confidence interval, RBC: red blood cell CI is based on Clopper-Pearson method.

All 6 (22%) patients who were transfusion free in ACTIVATE-T remained transfusion free in a long-term extension study. The median duration of response for the 6 patients was 17 months (range: 11.5+, 21.8+).

16 HOW SUPPLIED/STORAE AND HANDLING

How Supplied

PYRUKYND 28-Day Packs
Tablet Strength | Description | Imprint | NDC
5 mg | Round, blue, film-coated tablets | "M5" printed on one side | 71334-205-05
20 mg | Round, blue, film-coated tablets | "M20" printed on one side | 71334-210-20
50 mg | Oblong, blue, film-coated tablets | "M50" printed on one side | 71334-215-50

PYRUKYND Taper Packs
Tablet strength(s) | Blister Wallet Configuration | Tablet Description | Imprint | NDC
5 mg | 5 mg blister wallet containing 7 tablets | round, blue, film-coated tablets | "M5" printed on one side | 71334-220-11
20 mg and 5 mg | - 20 mg blister wallet containing 7 tablets - 5 mg blister wallet containing 7 tablets | round, blue, film-coated tablets round, blue, film-coated tablets | "M20" printed on one side "M5" printed on one side | 71334-225-12
50 mg and 20 mg | - 50 mg blister wallet containing 7 tablets - 20 mg blister wallet containing 7 tablets | oblong, blue, film- coated tablets round, blue, film-coated tablets | "M50"; printed on one side; "M20"; printed on one side | 71334-230-13

Storage

Store at 20°C to 25°C (68°F to 77°F) with excursions permitted between 15°C and 30°C (59°F and 86°F) [see USP Controlled Room Temperature]. Store the blister wallets in the original carton until use.

17 PATIENT COUNSELING INFORMATION

Advise the patient to read the FDA-approved patient labeling (Patient Information).

Acute Hemolysis with Abrupt Treatment Interruption

Inform patients of the risk of developing acute hemolysis and subsequent anemia following abrupt interruption or discontinuation of PYRUKYND. Inform patients to follow their healthcare provider’s instructions for discontinuing PYRUKYND. Upon discontinuing PYRUKYND, tell patients to immediately report any symptoms suggestive of acute hemolysis including jaundice, scleral icterus, dark urine, dizziness, confusion, fatigue, or shortness of breath to their healthcare provider for further evaluation [see Warnings and Precautions (5.1)].

Hepatocellular Injury in Another Condition

Inform patients of the risk of hepatocellular injury observed in patients with another condition during the first 6 months of treatment with mitapivat at a higher dose than that recommended for patients with PK deficiency. Tell patients to immediately report any symptoms suggestive of liver injury including jaundice, dark urine, right upper quadrant pain, nausea, vomiting, or loss of appetite to their healthcare provider for further evaluation [see Warnings and Precautions (5.2)].

Drug Interactions

Advise patients to inform their healthcare providers of all concomitant medications, including over-the-counter medications, vitamins, and herbal products [see Drug Interactions (7)].

Dosing and Storage Instructions

- Instruct patients to swallow the tablets whole with or without food and not to split, crush, chew, or dissolve the tablets.
- Advise patients if a dose of PYRUKYND is missed by 4 hours or less, to take the scheduled dose as soon as possible. If a dose of PYRUKYND is missed by more than 4 hours, advise the patient to not take a replacement dose and wait until the next scheduled dose.

PYRUKYND® is a registered trademark of Agios Pharmaceuticals, Inc.

© 2022 Agios Pharmaceuticals, Inc.

Manufactured for and Distributed by:

Agios Pharmaceuticals, Inc.

Cambridge, MA 02139

AG-PI-004

PATIENT INFORMATION
PYRUKYND [pye roo’ kind]
(mitapivat)
tablets, for oral use

What is PYRUKYND?

PYRUKYND is a prescription medicine used to treat low red blood cell counts caused by the early breakdown of red blood cells (hemolytic anemia) in adults with pyruvate kinase deficiency (PK Deficiency).

It is not known if PYRUKYND is safe and effective in children.

Before taking PYRUKYND, tell your healthcare provider about all your medical conditions, including if you:

- have liver problems.
- are pregnant or plan to become pregnant. It is not known if PYRUKYND will harm your unborn baby. Tell your healthcare provider right away if you become pregnant or think that you are pregnant during treatment with PYRUKYND.
- are breastfeeding or plan to breastfeed. It is not known if PYRUKYND passes into your breast milk. Talk to your healthcare provider about the best way to feed your baby during treatment with PYRUKYND.

Tell your healthcare provider about all the medicines that you take, including prescription and over-the- counter medicines, vitamins, and herbal supplements.

PYRUKYND and certain other medicines may affect each other causing side effects. PYRUKYND may affect the way other medicines work, and other medicines may affect how PYRUKYND works.

Know the medicines you take. Keep a list of them to show your healthcare provider or pharmacist when you get a new medicine.

How should I take PYRUKYND?

- Take PYRUKYND exactly as your healthcare provider tells you to take it.
- Take PYRUKYND with or without food.
- Swallow PYRUKYND tablets whole. Do not split, chew, crush, or dissolve the tablets.
- Do not change your dose or stop taking PYRUKYND without talking to your healthcare provider. Your healthcare provider will give you instructions for stopping PYRUKYND. See “What are the possible side effects of PYRUKYND?”
- If you miss a dose of PYRUKYND by 4 hours or less, take your dose as soon as possible. If more than 4 hours have passed since your regularly scheduled dose, wait for the next dose. Return to your normal schedule at the next dose.

What are the possible side effects of PYRUKYND? PYRUKYND may cause serious side effects, including:

- Rapid breakdown of red blood cells (acute hemolysis) has happened after suddenly interrupting or stopping treatment with PYRUKYND. You should not suddenly stop taking PYRUKYND. If you have to stop your treatment with PYRUKYND, your healthcare provider should monitor you closely. Tell your healthcare provider right away if you develop any signs or symptoms of breakdown of red blood cells including:

- yellowing of your skin or the whites of your eyes (jaundice)
- dark colored urine
- dizziness

- feeling tired
- shortness of breath
- confusion

- Liver injury has happened in people with another condition during the first 6 months of treatment with mitapivat when given at a dose higher than recommended for people with PK deficiency. Your healthcare provider will do blood tests to check your liver before you start treatment with PYRUKYND, monthly for the first 6 months of treatment, and as needed. Your healthcare provider may temporarily or permanently stop your treatment with PYRUKYND if you have abnormal liver tests. Tell your healthcare provider right away if you develop any signs or symptoms of liver problems including:

- yellowing of your skin or the whites of your eyes (jaundice)
- dark colored urine
- pain in the upper right side of your stomach area

- nausea
- vomiting
- loss of appetite

The most common side effects of PYRUKYND include:

- decrease in reproductive hormone (estrone) in men
- increased salt from uric acid (urate) blood test
- back pain

- decrease in reproductive hormone (estradiol) in men
- joint pain (arthralgia)

These are not all of the possible side effects of PYRUKYND.

Call your doctor for medical advice about side effects. You may report side effects to FDA at 1-800-FDA-1088.

How should I store PYRUKYND?

- Store PYRUKYND at room temperature between 68°F to 77°F (20°C to 25°C).
- Store the blister wallets in the original carton until use.

Keep PYRUKYND and all medicines out of the reach of children.

General information about the safe and effective use of PYRUKYND.

Medicines are sometimes prescribed for purposes other than those listed in a Patient Information leaflet. Do not use PYRUKYND for a condition for which it was not prescribed. Do not give PYRUKYND to other people, even if they have the same symptoms that you have. It may harm them. You can ask your healthcare provider or pharmacist for information about PYRUKYND that is written for healthcare professionals.

What are the ingredients in PYRUKYND?

Active ingredient: mitapivat

Inactive ingredients: croscarmellose sodium, mannitol, microcrystalline cellulose, and sodium stearyl fumarate.

The tablet film coating contains: FD&C Blue No. 2, hypromellose, lactose monohydrate, titanium dioxide, and triacetin.

The tablets printed with black ink contains: ammonium hydroxide, ferrosoferric oxide, isopropyl alcohol, n-butyl alcohol, propylene glycol, and shellac glaze.

Manufactured for and Distributed by:

Agios Pharmaceuticals, Inc.

Cambridge, MA 02139

PYRUKYND® is a trademark of Agios Pharmaceuticals, Inc.
© 2022 Agios Pharmaceuticals, Inc. All rights reserved.
For more information, visit www.pyrukynd.com or call 1-833-228-8474

This Patient Information has been approved by the U.S. Food and Drug Administration. Revised: 12/2025

PRINCIPAL DISPLAY PANEL - 5 mg Tablet Blister Pack Carton

NDC 71334-205-05
Do not use if seal
is broken or damaged

Rx Only

pyrukynd ®
(mitapivat) tablets
5 mg per tablet

56 tablets

Contains 4-week supply of PYRUKYND ®
(Four 7-day blister wallets with 14 tablets per wallet)
Swallow tablets whole. Do Not split, crush, chew, or dissolve the tablets.

PRINCIPAL DISPLAY PANEL - 20 mg Tablet Blister Pack Carton

NDC 71334-210-20
Do not use if seal
is broken or damaged

Rx Only

pyrukynd ®
(mitapivat) tablets
20 mg per tablet

56 tablets

Contains 4-week supply of PYRUKYND ®
(Four 7-day blister wallets with 14 tablets per wallet)
Swallow tablets whole. Do Not split, crush, chew, or dissolve the tablets.

PRINCIPAL DISPLAY PANEL - 50 mg Tablet Blister Pack Carton

NDC 71334-215-50
Do not use if seal
is broken or damaged

Rx Only

pyrukynd ®
(mitapivat) tablets
50 mg per tablet

56 tablets

Contains 4-week supply of PYRUKYND ®
(Four 7-day blister wallets with 14 tablets per wallet)
Swallow tablets whole. Do Not split, crush, chew, or dissolve the tablets.

PRINCIPAL DISPLAY PANEL - 5 mg Tablet Blister Pack Carton - 220-11

NDC 71334-220-11
Do not use if seal is broken or damaged

Rx Only

pyrukynd ®
(mitapivat) tablets

Week 1
5 mg per tablet

5 mg TAPER PACK

7 tablets

Swallow tablets whole.
Do Not split, crush, chew, or dissolve the tablets.

PRINCIPAL DISPLAY PANEL - 20 mg/5 mg Tablet Blister Pack Carton - 225-12

NDC 71334-225-12
Do not use if seal is broken or damaged

Rx Only

pyrukynd ®
(mitapivat) tablets

Week 1
20 mg per tablet

Week 2
5 mg per tablet

20 mg and 5 mg TAPER PACK

14 tablets

Contains two 7-day blister wallets with 7 tablets per wallet:
7 film-coated tablets of 20 mg per tablet (one tablet per day during week 1)
7 film-coated tablets of 5 mg per tablet (one tablet per day during week 2)

Swallow tablets whole.
Do Not split, crush, chew, or dissolve the tablets.

PRINCIPAL DISPLAY PANEL - 50 mg/20 mg Tablet Blister Pack Carton - 230-13

NDC 71334-230-13
Do not use if seal is broken or damaged

Rx Only

pyrukynd ®
(mitapivat) tablets

Week 1
50 mg per tablet

Week 2
20 mg per tablet

50 mg and 20 mg TAPER PACK

14 tablets

Contains two 7-day blister wallets with 7 tablets per wallet:
7 film-coated tablets of 50 mg per tablet (one tablet per day during week 1)
7 film-coated tablets of 20 mg per tablet (one tablet per day during week 2)

Swallow tablets whole.
Do Not split, crush, chew, or dissolve the tablets.